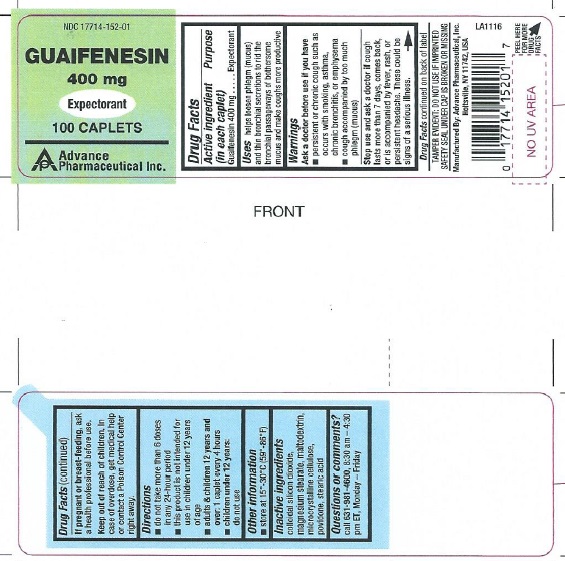 DRUG LABEL: Mucus Relief
NDC: 17714-152 | Form: TABLET
Manufacturer: Advance Pharmaceutical Inc.
Category: otc | Type: HUMAN OTC DRUG LABEL
Date: 20171030

ACTIVE INGREDIENTS: GUAIFENESIN 400 mg/1 1
INACTIVE INGREDIENTS: SILICON DIOXIDE; MAGNESIUM STEARATE; CELLULOSE, MICROCRYSTALLINE; MALTODEXTRIN; POVIDONE; STEARIC ACID

Guaifenesin Caplets, 400 mg

Active ingredient (in each tablet)

Guaifenesin 400 mg

Purpose

Expectorant

Uses

- helps loosen phlegm (mucus) and thin bronchial secretions to make coughs more productive to rid the bronchial passageway of bothersome mucus and make cough more productive

Warnings

ask a doctor before use if you have

- persistent or chronic cough such as occurs with smoking, asthma, chronic bronchitis or emphysema
- cough accompanied by excessive phlegm (mucus)

KEEP OUT OF REACH OF CHILDREN

In case of overdose, get medical help or contact a Poison Control Center right away.

IN CASE OF PREGNANCY OR BREAST FEEDING SECTION

ask a health professional before use

stop use and ask a doctor

if cough lasts more than 7 days, comes back, or is accompanied by fever, rash or persistent headache.These could be signs of serious illness

Directions:

- adults and children 12 years of age and over: take 1 tablet every 4 hours with a full glass of water while symptoms persist. Do not exceed 6 doses in 24 hours.
- children under 12 years: do not use

OTHER SAFETY INFORMATION

- store at 15°-30°C (59°-86°F)
- TAMPER EVIDENT: DO NOT USE IF IMPRINTED SAFETY SEAL UNDER CAP IS BROKEN OR MISSING

Inactive ingredients

colloidal silicon dioxide, magnesium stearate, microcrystalline cellulose, stearic acid, sodium starch glycolate

Questions or Comments

call 631-981-4600, 8.30 am-4.30 pm ET, Monday - Friday
TAMPER EVIDENT: DO NOT USE IF IMPRINTED SAFETY SEAL UNDER CAP IS BROKEN OR MISSING

Principal Display Panel

Guaifenesin 400 mg... Expectorant

NDC-17714-152-01 100 tabs